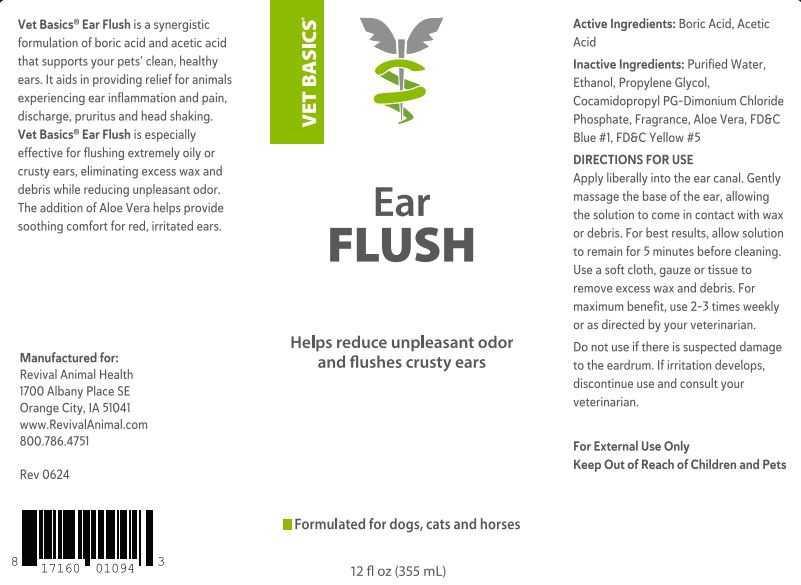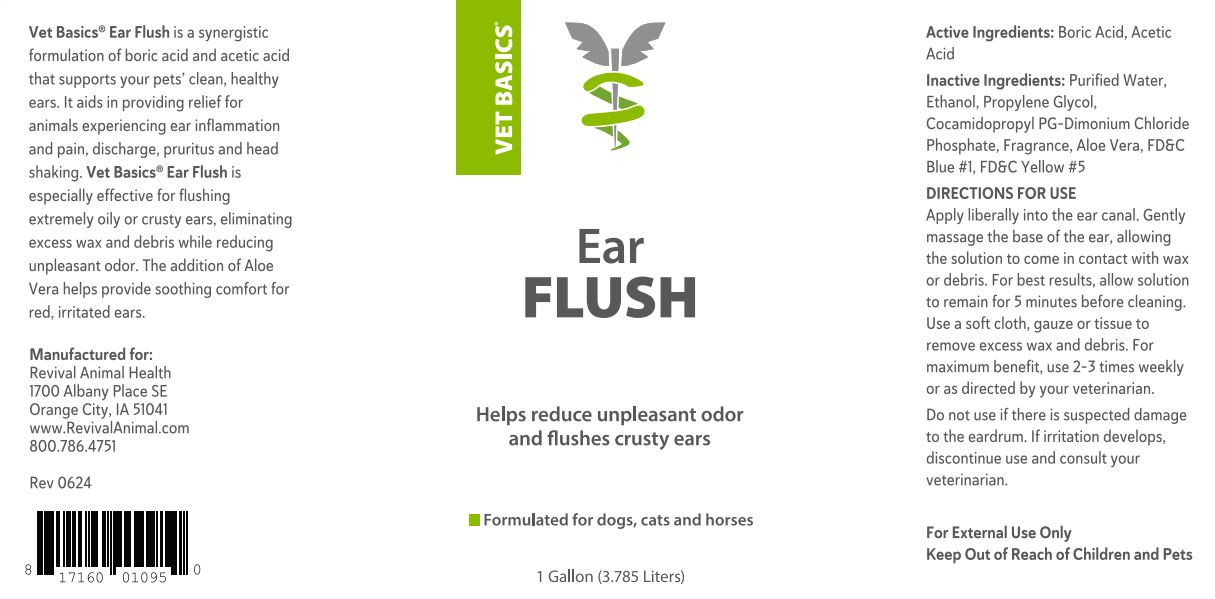 DRUG LABEL: Vet Basics Ear Flush
NDC: 86201-0006 | Form: RINSE
Manufacturer: Revival Animal Health
Category: animal | Type: OTC ANIMAL DRUG LABEL
Date: 20240730

ACTIVE INGREDIENTS: ACETIC ACID 404.98 mg/1 g; SODIUM BORATE 404.98 mg/1 g
INACTIVE INGREDIENTS: WATER; ALCOHOL; PROPYLENE GLYCOL; COCAMIDOPROPYL PROPYLENE GLYCOL-DIMONIUM CHLORIDE PHOSPHATE; LANOLIN; ALOE VERA LEAF; FD&C BLUE NO. 1; FD&C YELLOW NO. 5

INDICATIONS AND USAGE

Vet Basics® Ear Flush is a synergistic formulation of boric acid and acetic acid that supports your pets’ clean, healthy ears. It aids in providing relief for animals experiencing ear inflammation and pain, discharge, pruritus and head shaking. Vet Basics® Ear Flush is especially effective for flushing extremely oily or crusty ears, eliminating excess wax and debris while reducing unpleasant odor. The addition of Aloe Vera helps provide soothing comfort for red, irritated ears.

Manufactured for:
Revival Animal Health
1700 Albany Place SE
Orange City, IA 51041
www.RevivalAnimal.com
800.786.4751

Rev 0624

UPC 81716001094

Active Ingredients: Boric Acid, Acetic Acid

INACTIVE INGREDIENT

Ingredients: Purified Water, Ethanol, Propylene Glycol, Cocamidopropyl PG-Dimonium Chloride Phosphate, Fragrance, Aloe Vera, FD&C Blue #1, FD&C Yellow #5

DIRECTIONS FOR USE

Apply liberally into the ear canal. Gently massage the base of the ear, allowing the solution to come in contact with wax or debris. For best results, allow solution to remain for 5 minutes before cleaning. Use a soft cloth, gauze or tissue to remove excess wax and debris. For maximum benefit, use 2-3 times weekly or as directed by your veterinarian.

Do not use if there is suspected damage to the eardrum. If irritation develops, discontinue use and consult your veterinarian.

For External Use Only

Keep Out of Reach of Children and Pets

PACKAGE LABEL

Vet Basics® Ear Flush

Helps reduce unpleasant odor and flushes crusty ears

Formulated for dogs, cats and horses

12 fl oz (355 ml)

1 Gallon (3.785 Liters)